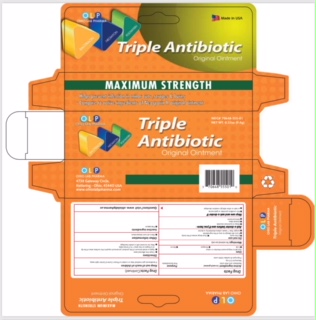 DRUG LABEL: OLP Triple Antibiotic
NDC: 70648-555 | Form: OINTMENT
Manufacturer: Ohio Lab Pharma
Category: otc | Type: HUMAN OTC DRUG LABEL
Date: 20181126

ACTIVE INGREDIENTS: BACITRACIN ZINC 400 [USP'U]/1 g; POLYMYXIN B SULFATE 5000 [USP'U]/1 g; NEOMYCIN SULFATE 3.5 mg/1 g
INACTIVE INGREDIENTS: PETROLATUM

Active Ingredients

- Bacitracin Zinc 400 units
- Neomycin Sulfate 3.5mg
- Polymyxin B Sulfate 5,000 units

Purpose

First aid antibiotic

USes

First aid to help prevent infection in minor:

- cuts
- scrapes
- burns

Warnings

- For external use only

Ask a doctor before use if you have

- serious burns
- deep or puncture wounds
- animal bites

Stop use and ask a doctor if

- condition persists or gets worse
- rash or other allergic reaction develops

do not use:

- do not use in the eyes
- do not apply over large areas of the body
- if you are allergic to any of the ingredients
- longer than one week unless directed by your doctor

Keep out of reach of children.

If swallowed, get medical help or contact a Poison Control Center right away.

Directions

- clean the affected area
- apply a small amount of this product (an amount equal tot the surface area of the tip of a finer) on the area 1 to 3 times daily
- may be covered with a sterile bandage

OTHER INFORMATION

- store at room temperature

Inactive Ingredient

Petrolatum

QUESTIONS

www.ohiolabpharma.us

PACKAGE LABEL

ORIGINAL OINTMENT

NET WEIGHT: 0.33OZ (9.4g)

NDC#70648-555-01